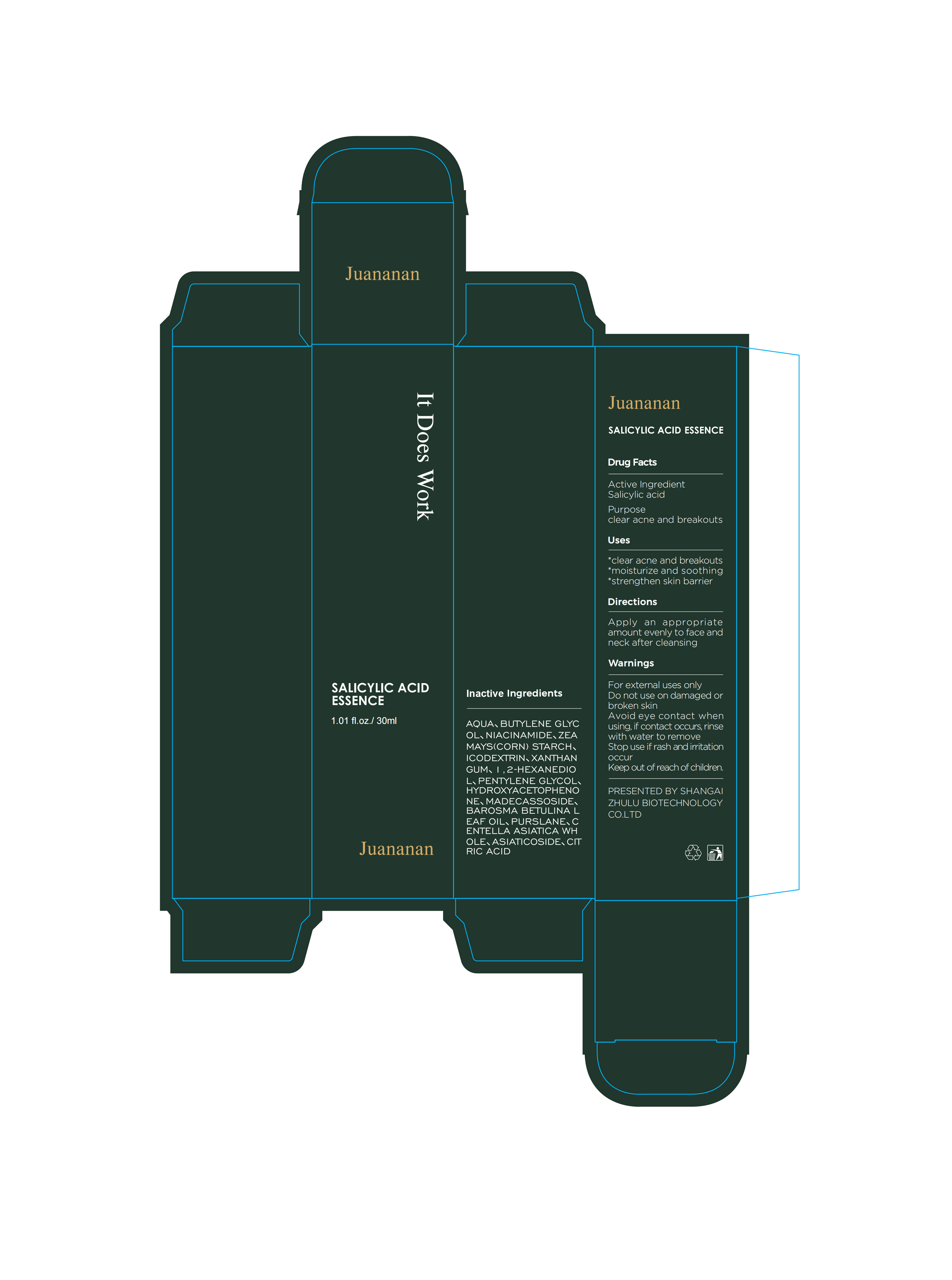 DRUG LABEL: Juananan SALICYLIC ACID ESSENCE
NDC: 87296-001 | Form: LIQUID
Manufacturer: Shanghai Zhulu Biotechnology Co., Ltd
Category: otc | Type: HUMAN OTC DRUG LABEL
Date: 20251221

ACTIVE INGREDIENTS: SALICYLIC ACID 1.4 g/100 g
INACTIVE INGREDIENTS: BAROSMA BETULINA LEAF OIL; ICODEXTRIN; NIACINAMIDE; MADECASSOSIDE; HYDROXYACETOPHENONE; ZEA MAYS (CORN) STARCH; XANTHAN GUM; 1,2-HEXANEDIOL; ASIATICOSIDE; CENTELLA ASIATICA WHOLE; PENTYLENE GLYCOL; AQUA; PURSLANE; CITRIC ACID; BUTYLENE GLYCOL

Active Ingredient

SALICYLIC ACID 1.4%

Purpose

Clear acne and breakouts

Inactive Ingredients

AQUA、

BUTYLENE GLYCOL、

NIACINAMIDE、

ZEA MAYS (CORN) STARCH、

ICODEXTRIN、

XANTHAN GUM、

1,2-HEXANEDIOL、

PENTYLENE GLYCOL、

YDROXYACETOPHENONE、

MADECASSOSIDE、

BAROSMA BETULINA LEAF OIL、

PURSLANE、

CENTELLA ASIATICA WHOLE、

ASIATICOSIDE、

CITRIC ACID

Uses

* Clear acne and breakouts
* Moisturize and soothing
* Strengthen skin barrier

DOSAGE AND ADMINISTRATION

Apply an appropriate amount evenly to face and neck after cleansing

Directions

Apply an appropriate amount evenly to face and neck after cleansing

Keep out of reach of children.

Warnings

For external uses only Do not use on damaged or broken skin

Avoid eye contact when using, if contact occurs, rinse with water to remove

Stop use if rash and irritation occur Keep out of reach of children.